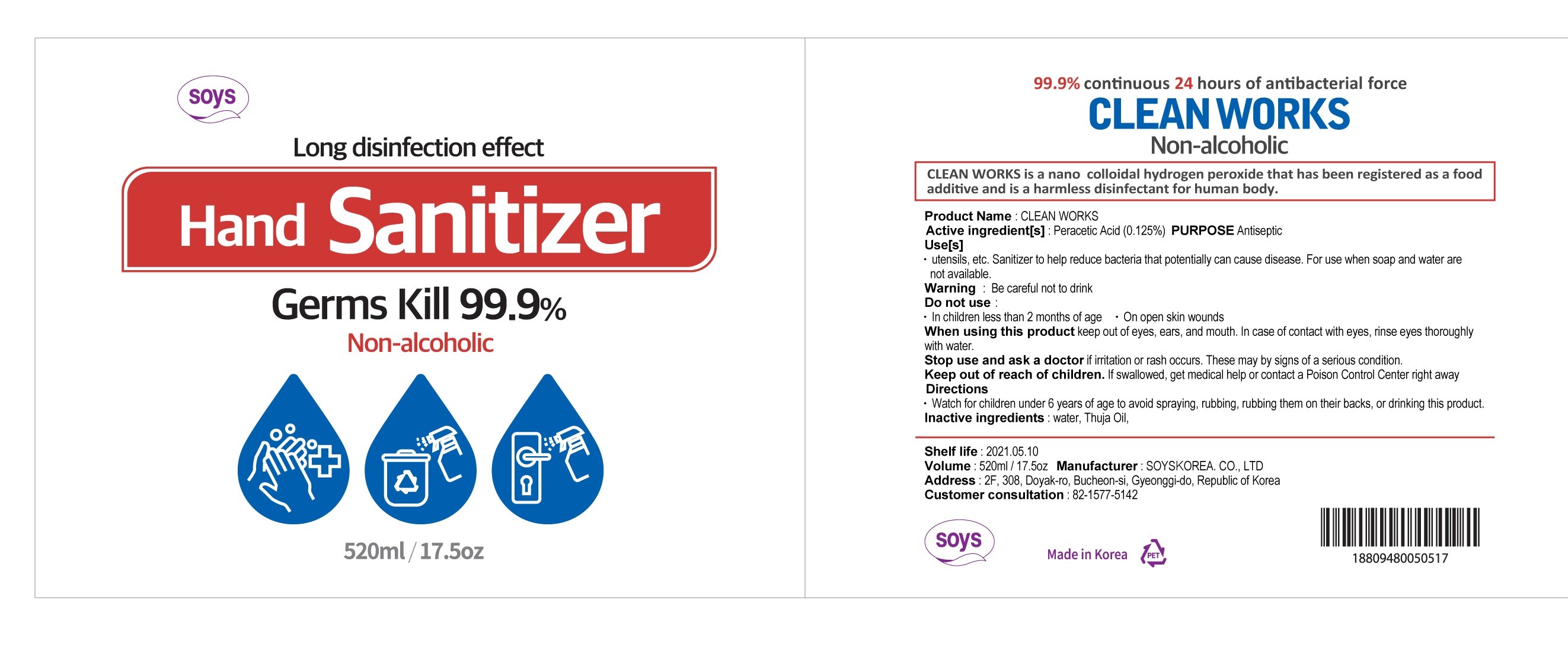 DRUG LABEL: CLEAN WORKS
NDC: 77166-201 | Form: LIQUID
Manufacturer: SOYSKOREA CO., LTD
Category: otc | Type: HUMAN OTC DRUG LABEL
Date: 20200430

ACTIVE INGREDIENTS: PERACETIC ACID 0.125 g/100 mL
INACTIVE INGREDIENTS: CEDAR LEAF OIL; WATER

Active Ingredient

Peracetic Acid 0.125%

Purpose

Antiseptic

Use

utensils, etc. Sanitizer to help reduce bacteria that potentially can cause disease. For use when soap and water are not available.

Warning

Be careful not to drink

Do not use

In children less than 2 months of age

On open skin wounds

When using this product

keep out of eyes, ears, and mouth. In case of contact with eyes, rinse eyes thorough with water.

Stop use and ask a doctor

if irritation or rash occurs. These may by signs of a serious condition.

Keep out of reach of children.

If swallowed, get medical help or contact a Poison Control Center right away

Directions

Watch for children under 6 years of age to avoid spraying, rubbing, rubbing them on their backs, or drinking this product.

Inactive ingredients

Water, Thuja Oil